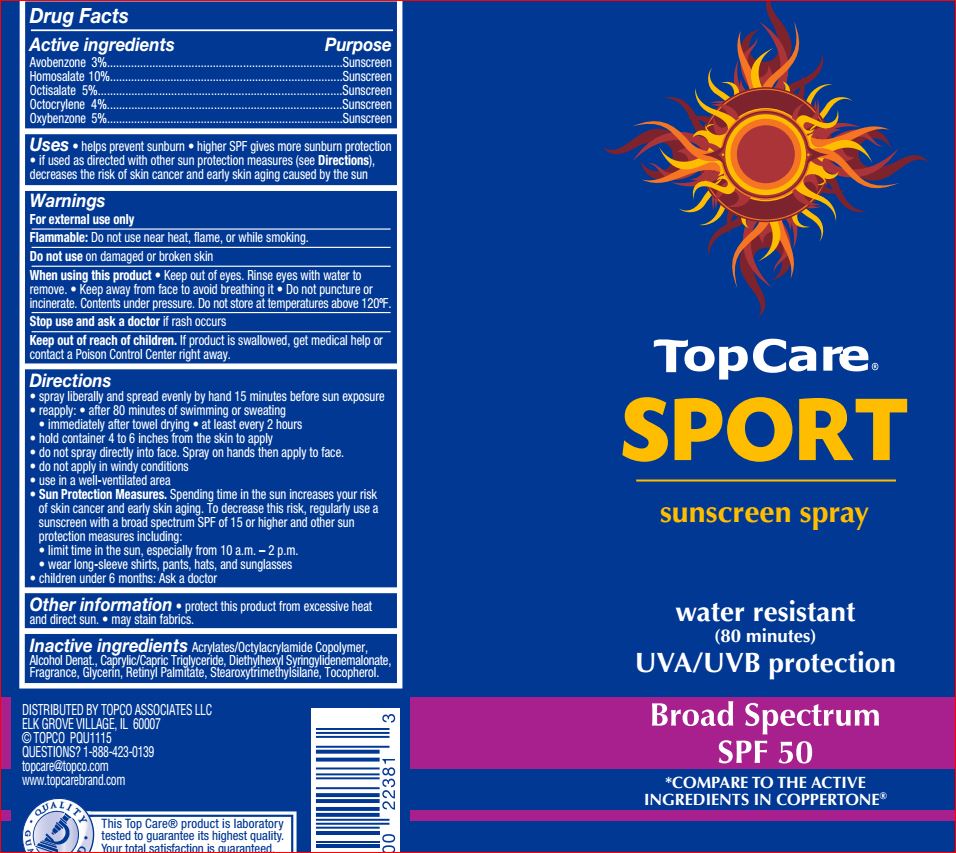 DRUG LABEL: Sport Sunscreen SPF 50
NDC: 36800-726 | Form: SPRAY
Manufacturer: TopCare
Category: otc | Type: HUMAN OTC DRUG LABEL
Date: 20180717

ACTIVE INGREDIENTS: Avobenzone 3 g/100 g; Homosalate 10 g/100 g; Octisalate 5 g/100 g; Octocrylene 4 g/100 g; Oxybenzone 5 g/100 g
INACTIVE INGREDIENTS: ALCOHOL; STEAROXYTRIMETHYLSILANE; MEDIUM-CHAIN TRIGLYCERIDES; Diethylhexyl Syringylidenemalonate; Glycerin; VITAMIN A PALMITATE; Tocopherol

Drug Facts

Active ingredients Purpose
Avobenzone 3%.......................................................................................Sunscreen
Homosalate 10%.....................................................................................Sunscreen
Octisalate 5%..........................................................................................Sunscreen
Octocrylene 4%.......................................................................................Sunscreen
Oxybenzone 5%.......................................................................................Sunscreen

INDICATIONS AND USAGE

Uses • helps prevent sunburn • higher SPF gives more sunburn protection
• retains SPF after 80 minutes of activity in the water or sweating • provides
moderate protection against sunburn

Warnings
Flammable: Do not use near heat, flame, or while smoking.
For external use only
Do not use on damaged or broken skin.
When using this product keep out of eyes. Rinse with water to remove.
Stop use and ask a doctor if • rash or irritation develops and last

Avoid spraying in eyes. Contents under pressure. Do not puncture or incinerate. Do
not store at temperature above 120°F

Keep out of reach of children. If product is swallowed, get medical help or contact a Poison Control Center right away

DOSAGE AND ADMINISTRATION

Directions • Apply liberally 15 minutes before sun exposure and as needed.
• Children under 6 months of age: ask a doctor. • Reapply: • after 80 minutes of
swimming or sweating • immediately after towel drying • at least every 2 hours.
• Sun Protection Measures. Spending time in the sun increases your risk of skin
cancer and early skin aging. To decrease this risk, regularly use a sunscreen with a
Broad Spectrum SPF value of 15 or higher and other sun protection measures
including: • limit time in the sun, especially from 10 a.m.-2 p.m. • wear
long-sleeved shirts, pants, hats, and sunglasses. • Hold container 4 to 6 inches
from the skin to apply. • Do not spray directly into face. Spray on hands then apply
to face. • Do not apply in windy conditions. • Use in a well-ventilated area. • For
sunscreen use: • apply to all skin exposed to the sun. • Reapply as needed or after
towel drying, swimming, or sweating.

Other information • protect the product in this container from excessive heat and direct sun • may stain fabrics.

Inactive ingredients Acrylates/Octylacrylamide Copolymer, Alcohol
Denat., Caprylic/Capric Triglyceride, Diethylhexyl Syringylidenemalonate,
Fragrance, Glycerin, Retinyl Palmitate, Stearoxytrimethylsilane, Tocopherol.